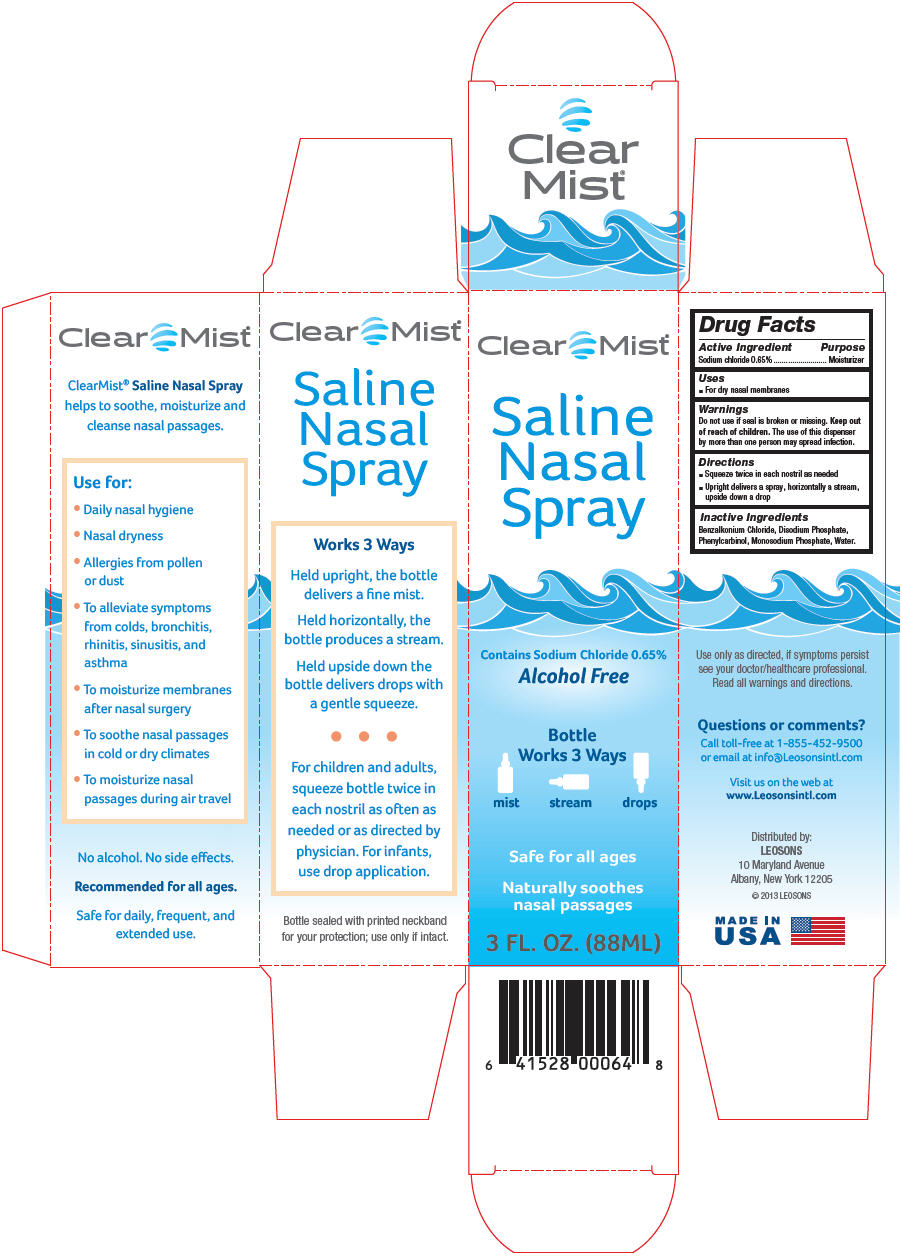 DRUG LABEL: Clear Mist
NDC: 69626-0064 | Form: LIQUID
Manufacturer: Leosons Overseas Corp
Category: otc | Type: HUMAN OTC DRUG LABEL
Date: 20241118

ACTIVE INGREDIENTS: SODIUM CHLORIDE 6.5 mg/1 mL
INACTIVE INGREDIENTS: BENZALKONIUM CHLORIDE; SODIUM PHOSPHATE, DIBASIC, ANHYDROUS; SODIUM PHOSPHATE, MONOBASIC, ANHYDROUS; BENZYL ALCOHOL; WATER

Clear Mist (Sheffield Pharmaceutical)

Drug Facts

Active ingredient & Purpose

Active ingredients | Purpose
Sodium chloride 0.65% | Moisturizer

Uses

- For dry nasal membranes

Warnings

Do not use

- if seal is broken or missing.

Keep out of reach of children.

The use of this dispenser by more than one person may spread infection.

Directions

- squeeze twice in each nostril as needed
- upright delivers a spray, horizontally a stream, upside down a drop

Inactive Ingredients

benzalkonium chloride, disodium phosphate, phenylcarbinol, monosodium phosphate, water.

Questions or comments?

Call toll-free at 1-855-452-9500 or email at info@Leosonsintl.com

Distributed by:

LEOSONS

10 Maryland Avenue
Albany, New York 12205

PRINCIPAL DISPLAY PANEL

Clear Mist®

Saline
Nasal
Spray

Contains Sodium Chloride 0.65%
Alcohol Free

Bottle
Works 3 Ways

mist stream drops

Safe for all ages

Naturally soothes
nasal passages